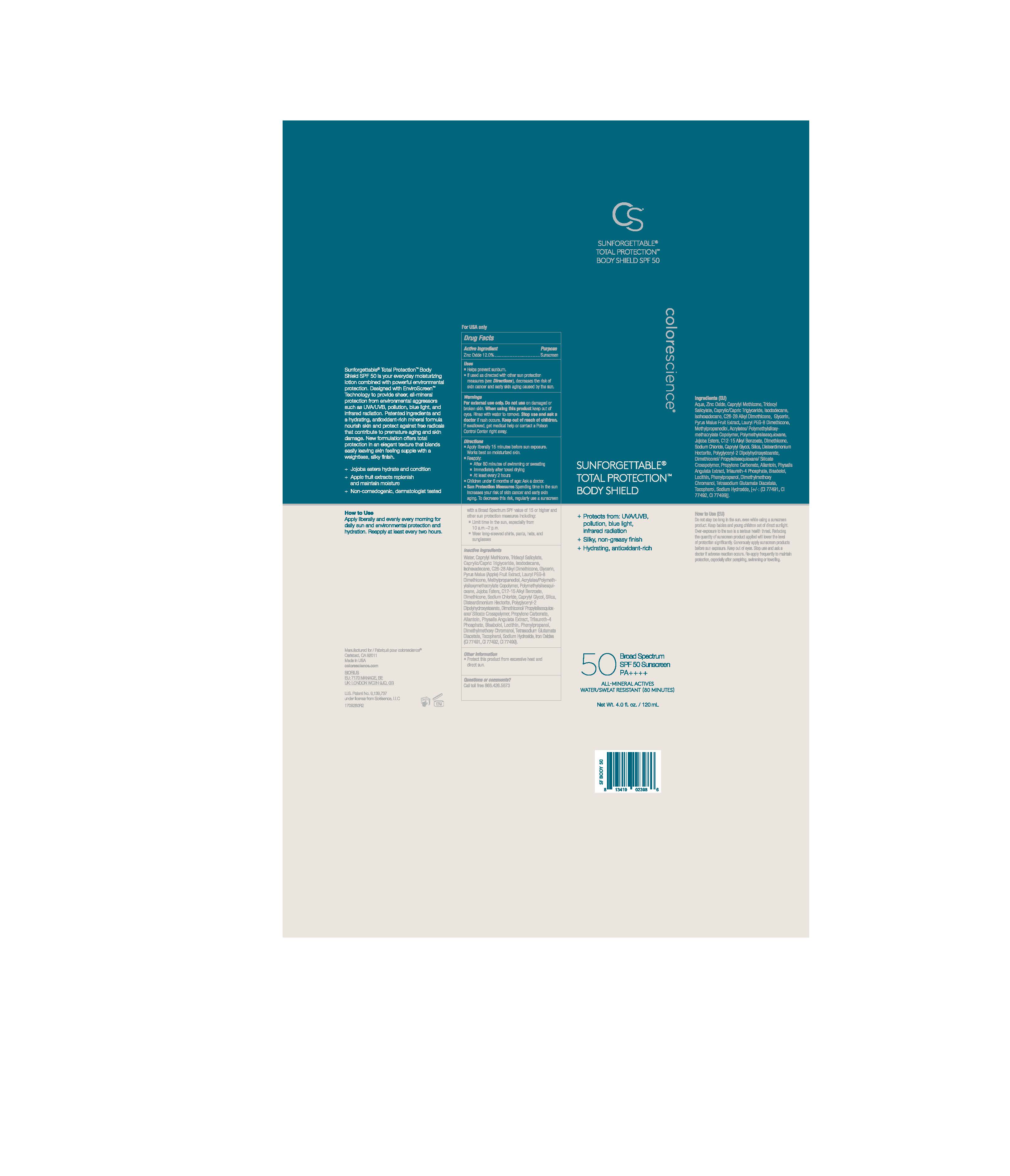 DRUG LABEL: Sunforgettable Total Protection Body Shield
NDC: 68078-055 | Form: LOTION
Manufacturer: Colorescience
Category: otc | Type: HUMAN OTC DRUG LABEL
Date: 20251015

ACTIVE INGREDIENTS: ZINC OXIDE 135.6 mg/1 mL
INACTIVE INGREDIENTS: ISOHEXADECANE; PROPYLENE CARBONATE; PHENYLPROPANOL; METHYLPROPANEDIOL; CAPRYLYL GLYCOL; HYDROLYZED JOJOBA ESTERS (ACID FORM); TOCOPHEROL; TRIDECYL SALICYLATE; DIMETHYLMETHOXY CHROMANOL; ALLANTOIN; .ALPHA.-BISABOLOL, (+)-; SILICON DIOXIDE; TRILAURETH-4 PHOSPHATE; ISODODECANE; SODIUM HYDROXIDE; WATER; DIMETHICONOL/PROPYLSILSESQUIOXANE/SILICATE CROSSPOLYMER (450000000 MW); SODIUM CHLORIDE; TREMELLA FUCIFORMIS FRUITING BODY; MALTODEXTRIN; ALKYL (C12-15) BENZOATE; DISODIUM LAURIMINODIPROPIONATE TOCOPHERYL PHOSPHATES; ISOCETETH-10; DISTEARDIMONIUM HECTORITE; POLYMETHYLSILSESQUIOXANE (11 MICRONS); PHYSALIS ANGULATA; POLYGLYCERYL-2 DIPOLYHYDROXYSTEARATE; LECITHIN, SOYBEAN; TETRASODIUM GLUTAMATE DIACETATE; GLYCERIN

Sunforgettable Total Protection Body Shield